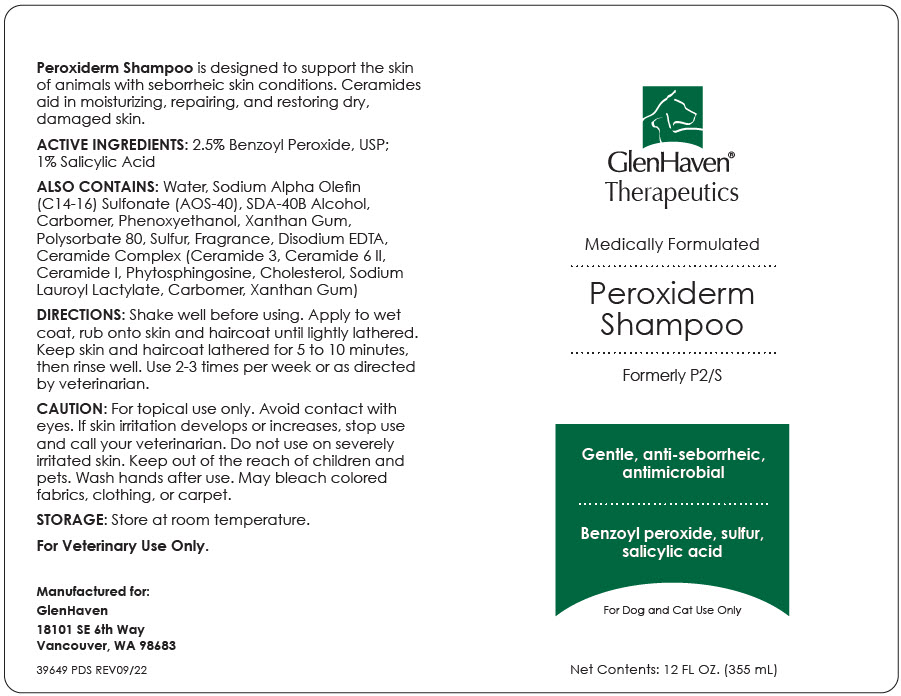 DRUG LABEL: Peroxiderm
NDC: 70782-626 | Form: SHAMPOO, SUSPENSION
Manufacturer: GlenHaven LLC
Category: animal | Type: OTC ANIMAL DRUG LABEL
Date: 20231110

ACTIVE INGREDIENTS: BENZOYL PEROXIDE 25 mg/1 mL; SALICYLIC ACID 1 mg/1 mL

Peroxiderm Shampoo

VETERINARY INDICATIONS

Peroxiderm Shampoo is designed to support the skin of animals with seborrheic skin conditions. Ceramides aid in moisturizing, repairing, and restoring dry, damaged skin.

DESCRIPTION

ACTIVE INGREDIENTS: 2.5% Benzoyl Peroxide, USP; 1% Salicylic Acid

ALSO CONTAINS: Water, Sodium Alpha Olefin (C14-16) Sulfonate (AOS-40), SDA-40B Alcohol, Carbomer, Phenoxyethanol, Xanthan Gum, Polysorbate 80, Sulfur, Fragrance, Disodium EDTA, Ceramide Complex (Ceramide 3, Ceramide 6 II, Ceramide I, Phytosphingosine, Cholesterol, Sodium Lauroyl Lactylate, Carbomer, Xanthan Gum)

DOSAGE AND ADMINISTRATION

DIRECTIONS: Shake well before using. Apply to wet coat, rub onto skin and haircoat until lightly lathered. Keep skin and haircoat lathered for 5 to 10 minutes, then rinse well. Use 2-3 times per week or as directed by veterinarian.

WARNINGS

CAUTION: For topical use only. Avoid contact with eyes. If skin irritation develops or increases, stop use and call your veterinarian. Do not use on severely irritated skin. Keep out of the reach of children and pets. Wash hands after use. May bleach colored fabrics, clothing, or carpet.

STORAGE: Store at room temperature.

For Veterinary Use Only.

Manufactured for:
GlenHaven
18101 SE 6th Way
Vancouver, WA 98683

39649 PDS REV09/22

PRINCIPAL DISPLAY PANEL - 355 mL Bottle Label

GlenHaven®
Therapeutics

Medically Formulated

Peroxiderm
Shampoo

Formerly P2/S

Gentle, anti-seborrheic,
antimicrobial

Benzoyl peroxide, sulfur,
salicylic acid

For Dog and Cat Use Only

Net Contents: 12 FL OZ. (355 mL)